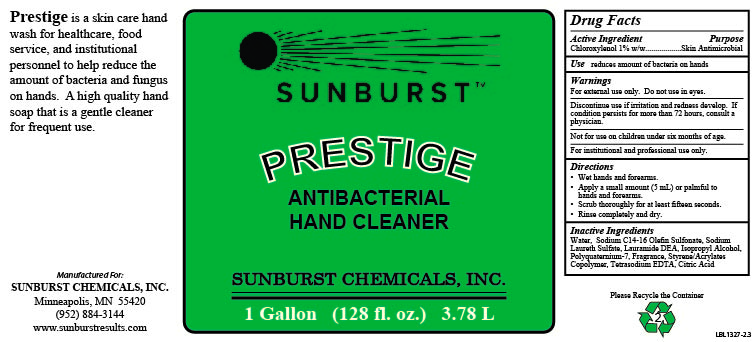 DRUG LABEL: Prestige
NDC: 63621-335 | Form: SOAP
Manufacturer: Sunburst Chemicals, Inc.
Category: otc | Type: HUMAN OTC DRUG LABEL
Date: 20240321

ACTIVE INGREDIENTS: CHLOROXYLENOL 10 mg/1 mL
INACTIVE INGREDIENTS: WATER; LAURAMINE OXIDE; EDETATE SODIUM; ISOPROPYL ALCOHOL; POLYQUATERNIUM-7 (70/30 ACRYLAMIDE/DADMAC; 1600000 MW); CITRIC ACID MONOHYDRATE; SODIUM C14-16 OLEFIN SULFONATE; SODIUM LAURETH SULFATE

Prestige

Active Ingredient

Chloroxylenol 1% w/w

Purpose

Skin Antimicrobial

Use

reduces amount of bacteria on hands

Warnings

For external use only. Do not use in eyes.

Discontinue use if irritation and redness develop. If condition persists for more than 72 hours, consult a physician.

KEEP OUT OF REACH OF CHILDREN

Not for use on children under 6 months of age.

For institutional and professional use only.

Directions

- Wet hands and forearms.
- Apply a small amount (5 mL) or palmful to hands and forearms.
- Scrub thoroughly for at least fifteen seconds.
- Rinse completely and dry.

Inactive Ingredients

Water, Sodium C14-16 Olefin Sulfonate, Sodium Laureth Sulfate, Lauramide DEA, Isopropyl Alcohol, Polyquaternium-7, Fragrance, Styrene/Acrylates Copolymer, Tetrasodium EDTA, Citric Acid